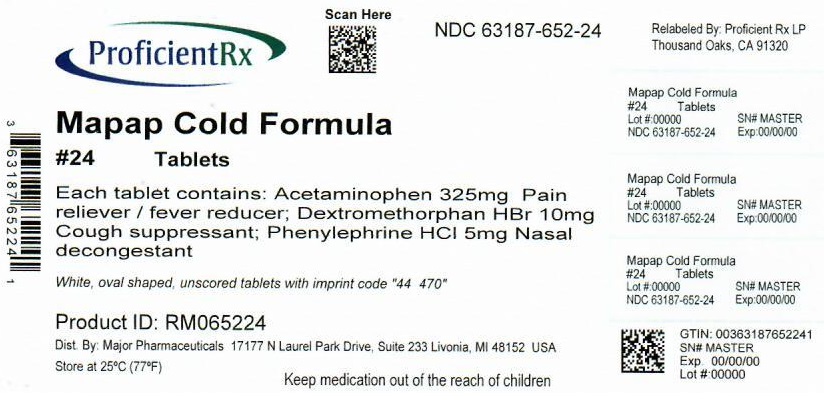 DRUG LABEL: Multi-Symptom Mapap Cold Formula
NDC: 63187-652 | Form: TABLET, FILM COATED
Manufacturer: Proficient Rx LP
Category: otc | Type: HUMAN OTC DRUG LABEL
Date: 20231101

ACTIVE INGREDIENTS: ACETAMINOPHEN 325 mg/1 1; DEXTROMETHORPHAN HYDROBROMIDE 10 mg/1 1; PHENYLEPHRINE HYDROCHLORIDE 5 mg/1 1
INACTIVE INGREDIENTS: STARCH, CORN; TALC; TITANIUM DIOXIDE; MICROCRYSTALLINE CELLULOSE; CROSCARMELLOSE SODIUM; MAGNESIUM STEARATE; POLYETHYLENE GLYCOL, UNSPECIFIED; POLYVINYL ALCOHOL, UNSPECIFIED; POVIDONE, UNSPECIFIED

Major 44-470C-CMS

Active ingredients (in each caplet)

Acetaminophen 325 mg
Dextromethorphan HBr 10 mg
Phenylephrine HCl 5 mg

Purpose

Pain reliever/fever reducer
Cough suppressant
Nasal decongestant

Uses

- temporarily relieves these common cold/flu symptoms:
  - minor aches and pains
  - headache
  - nasal congestion
  - cough
  - sore throat
  - sinus congestion and pressure
- helps clear nasal passages
- promotes nasal and sinus drainage
- temporarily reduces fever

Warnings

Liver warning: This product contains acetaminophen. The maximum daily dose of ths product is 10 caplets (3,250 mg acetaminophen) in 24 hours. Severe liver damage may occur if you take:

- more than 4,000 mg of acetaminophen in 24 hours
- with other drugs containing acetaminophen
- 3 or more alcoholic drinks every day while using this product

Sore throat warning: If sore throat is severe, persists for more than 2 days, is accompanied or followed by fever, headache, rash, nausea, or vomiting, consult a doctor promptly.

Do not use

- with any other drug containing acetaminophen (prescription or nonprescription). If you are not sure whether a drug contains acetaminophen, ask a doctor or pharmacist.
- if you are now taking a prescription monoamine oxidase inhibitor (MAOI) (certain drugs for depression, psychiatric or emotional conditions, or Parkinson's disease) or for 2 weeks after stopping the MAOI drug. If you do not know if your prescription drug contains an MAOI, ask a doctor or pharmacist before using this product.

Ask a doctor before use if you have

- liver disease
- diabetes
- heart disease
- high blood pressure
- thyroid disease
- trouble urinating due to an enlarged prostate gland
- persistent or chronic cough such as occurs with smoking, asthma, or emphysema
- cough that occurs with too much phlegm (mucus)

Ask a doctor or pharmacist before use if you are

taking the blood thinning drug warfarin.

When using this product

do not exceed recommended dosage.

Stop use and ask a doctor if

- nervousness, dizziness, or sleeplessness occur
- pain, nasal congestion, or cough gets worse or lasts more than 7 days
- new symptoms occur
- fever gets worse or lasts more than 3 days
- redness or swelling is present
- cough comes back or occurs with rash or headache that lasts. These could be signs of a serious condition.

If pregnant or breast-feeding,

ask a health professional before use.

Keep out of reach of children.

Overdose warning: Taking more than the recommended dose (overdose) may cause liver damage. In case of overdose, get medical help or contact a Poison Control Center (1-800-222-1222) right away. Quick medical attention is critical for adults as well as for children even if you do not notice any signs or symptoms.

Directions

- do not take more than directed (see overdose warning)
- adults and children 12 years and over:
  - take 2 caplets every 4 hours
  - swallow whole - do not crush, chew, or dissolve
  - do not take more than 10 caplets in 24 hours
- children under 12 years: ask a doctor

Other information

- store at 25ºC (77ºF); excursions permitted between 15º-30ºC (59º-86º)
- see end flap for expiration date and lot number

Inactive ingredients

corn starch, croscarmellose sodium, crospovidone, flavor, magnesium stearate, microcrystalline cellulose, polyethylene glycol, polyvinyl alcohol, povidone, silica gel, stearic acid, sucralose, talc, titanium dioxide

Questions or comments?

(800) 616-2471

Principal Display Panel

Major®

NDC 63187-652-24

MULTI-SYMPTOM
Mapap®
COLD FORMULA
CAPLETS

ASPIRIN FREE
ACETAMINOPHEN
DEXTROMETHORPHAN HBr
PHENYLEPHRINE HCl

DAYTIME • NON-DROWSY

Pain Reliever / Fever Reducer
Cough Suppressant • Nasal Decongestant

For Relief of: Fever, Headache,
Sore Throat, Nasal Congestion, Coughing

24 CAPLETS with Cool Blast Flavor

Compare to active ingredients in TYLENOL® Cold Multi-Symptom Daytime*

*This product is not manufactured or distributed by McNeil Consumer Healthcare, owner of the registered trademark Tylenol® Cold Multi-Symptom Daytime. 50844 REV0213D47008

Distributed by MAJOR® PHARMACEUTICALS
31778 Enterprise Drive
Livonia, MI 48150 USA M-17 Rev.02/13

Relabeled by Proficient Rx LP

Thousand Oaks, CA 91320

TAMPER EVIDENT: DO NOT USE IF CARTON IS OPENED OR IF BLISTER UNIT IS TORN, BROKEN OR SHOWS ANY SIGNS OF TAMPERING.